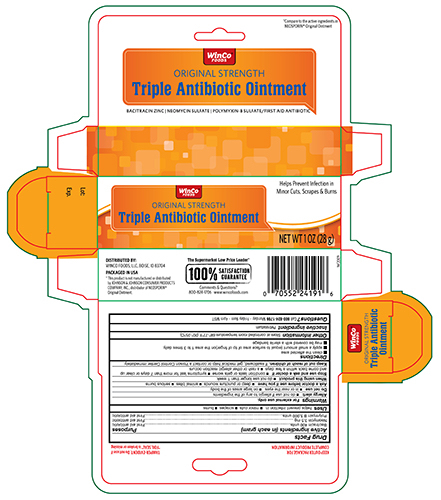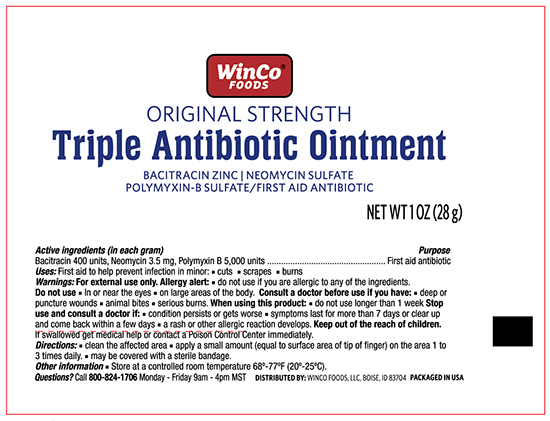 DRUG LABEL: WinCo Original Strength Triple Antibiotic
NDC: 67091-274 | Form: OINTMENT
Manufacturer: WinCo Foods, LLC
Category: otc | Type: HUMAN OTC DRUG LABEL
Date: 20241121

ACTIVE INGREDIENTS: BACITRACIN ZINC 400 [iU]/1 g; NEOMYCIN SULFATE 3.5 mg/1 g; POLYMYXIN B SULFATE 5000 [iU]/1 g
INACTIVE INGREDIENTS: PETROLATUM

Winco Triple Antibiotic Ointment 1 oz. NBE Neosporin Original

Active ingredients (in each gram) Purpose

Bacitracin zinc 400 units................................................................................................... First aid antibiotic

Neomycin sulfate 3.5 mg................................................................................................... First aid antibiotic

Polymyxin B sulfate 5,000 units........................................................................................ First aid antiobiotic

Uses

first aid to help prevent infection in minor:

- cuts
- scrapes
- burns

Warnings

For external use only

Do not use

- if you are allergic to any of the ingredients
- in the eyes
- over large areas of the body

Ask a doctor before use if you have

- deep or puncture wounds
- animal bites
- serious burns

Stop use and ask a doctor if

- you need to use longer than 1 week
- the condition persits or gets worse
- rash or other allergic reaction develops

KEEP OUT OF REACH OF CHILDREN

Keep out of children. If swallowed, get medical help or contact a Poison Control Center right away.

Directions

- clean the affected area
- apply a small amount of this product (an amount equal to the surface area of the tip of a finger) on the area 1 to 3 times daily
- may be covered with a sterile bandage

Inactive ingredients

petrolatum

DOSAGE AND ADMINISTRATION

DISTRIBUTED BY:

WINCO FOODS, LLC

BOISE, ID 83704

PACKAGE LABEL

WinCo Foods

Triple Antibiotic Ointment

Bacitracin Zinc , Neomycin Sulfate, Polymixin- B Sulfate

First Aid Antibiotic

NET WT 1 OZ (28g)

PACKAGE LABEL

Winco Foods

Triple Antibiotic Ointment

Bacitracin Zinc, Neomycin Sulfate, Polymixin B Sulfate

NET WT 1 OZ (28g)